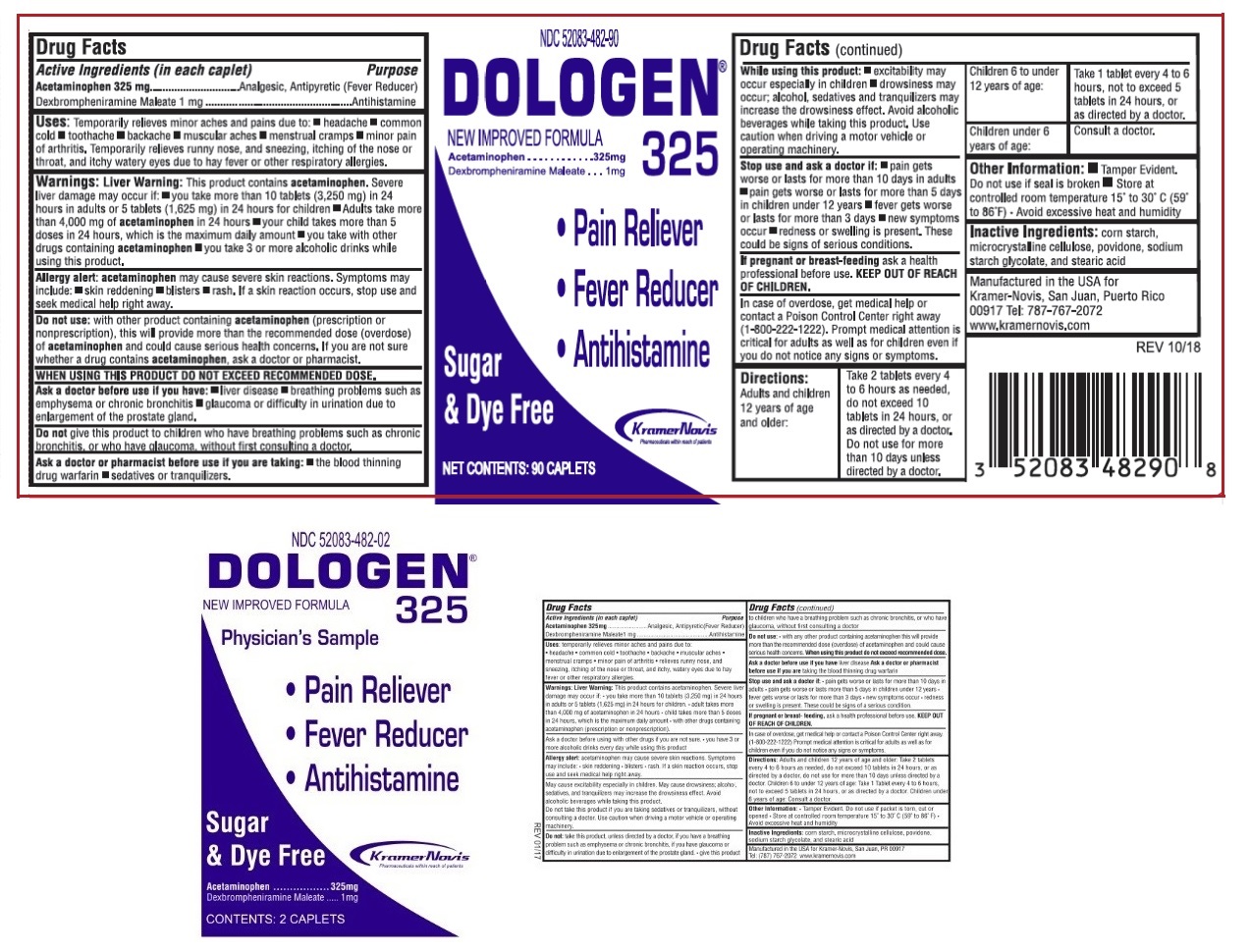 DRUG LABEL: Dologen 325
NDC: 52083-482 | Form: TABLET
Manufacturer: Kramer Novis
Category: otc | Type: HUMAN OTC DRUG LABEL
Date: 20181214

ACTIVE INGREDIENTS: ACETAMINOPHEN 325 mg/1 1; DEXBROMPHENIRAMINE MALEATE 1 mg/1 1
INACTIVE INGREDIENTS: STARCH, CORN; MICROCRYSTALLINE CELLULOSE; POVIDONE K30; SODIUM STARCH GLYCOLATE TYPE A CORN; STEARIC ACID

DOLOGEN® 325

Active Ingredients (in each caplet)

Acetaminophen 325 mg

Dexbrompheniramine Maleate 1 mg

Purpose

Analgesic, Antipyretic (Fever Reducer)

Antihistamine

Uses:

Temporarily relieves minor aches and pains due to: • headache • common cold • toothache • backache • muscular aches • menstrual cramps • minor pain of arthritis. Temporarily relieves runny nose, and sneezing, itching of the nose or throat, and itchy watery eyes due to hay fever or other respiratory allergies.

Warnings:

Liver Warning: This product contains acetaminophen. Severe liver damage may occur if: • you take more than 10 tablets (3,250 mg) in 24 hours in adults or 5 tablets (1,625 mg) in 24 hours for children • Adults take more than 4,000 mg of acetaminophen in 24 hours • your child takes more than 5 doses in 24 hours, which is the maximum daily amount • you take with other drugs containing acetaminophen • you take 3 or more alcoholic drinks while using this product.

Allergy alert: acetaminophen may cause severe skin reactions. Symptoms may include: • skin reddening • blisters • rash. If a skin reaction occurs, stop use and seek medical help right away.

Do not use : with other product containing acetaminophen (prescription or nonprescription), this will provide more than the recommended dose (overdose) of acetaminophen and could cause serious health concerns. If you are not sure whether a drug contains acetaminophen, ask a doctor or pharmacist.

WHEN USING THIS PRODUCT DO NOT EXCEED RECOMMENDED DOSE.

Ask a doctor before use if you have: • liver disease • breathing problems such as emphysema or chronic bronchitis • glaucoma or difficulty in urination due to enlargement of the prostate gland.

Do not give this product to children who have breathing problems such as chronic bronchitis, or who have glaucoma, without first consulting a doctor.

Ask a doctor or pharmacist before use if you are taking: • the blood thinning drug warfarin • sedatives or tranquilizers.

While using this product: • excitability may occur especially in children • drowsiness may occur; alcohol, sedatives and tranquilizers may increase the drowsiness effect. Avoid alcoholic beverages while taking this product. Use caution when driving a motor vehicle or operating machinery.

Stop use and ask a doctor if: • pain gets worse or lasts for more than 10 days in adults • pain gets worse or lasts for more than 5 days in children under 12 years • fever gets worse or lasts for more than 3 days • new symptoms occur • redness or swelling is present. These could be signs of serious conditions.

If pregnant or breast-feeding ask a health professional before use.

KEEP OUT OF REACH OF CHILDREN.

In case of overdose, get medical help or contact a Poison Control Center right away (1-800-222-1222). Prompt medical attention is critical for adults as well as for children even if you do not notice any signs or symptoms.

Directions

Adults and children 12 years of age and older: | Take 2 tablets every 4 to 6 hours as needed, do not exceed 10 tablets in 24 hours, or as directed by a doctor. Do not use for more than 10 days unless directed by a doctor.
Children 6 to under 12 years of age: | Take 1 tablet every 4 to 6 hours, not to exceed 5 tablets in 24 hours, or as directed by a doctor.
Children under 6 years of age: | Consult a doctor.

Other Information:

• Tamper Evident. Do not use if seal is broken.

• Store at controlled room temperature 15° to 30°C (59° to 86°F). Avoid excessive heat and humidity.

Inactive Ingredients:

corn starch, microcrystalline cellulose, povidone, sodium starch glycolate, and stearic acid

NEW IMPROVED FORMULA

- Pain Reliever
- Fever Reducer
- Antihistamine

Sugar & Dye Free

Manufactured in the USA for

Kramer-Novis, San Juan, Puerto Rico 00917 Tel: 787-767-2072

www.kramernovis.com